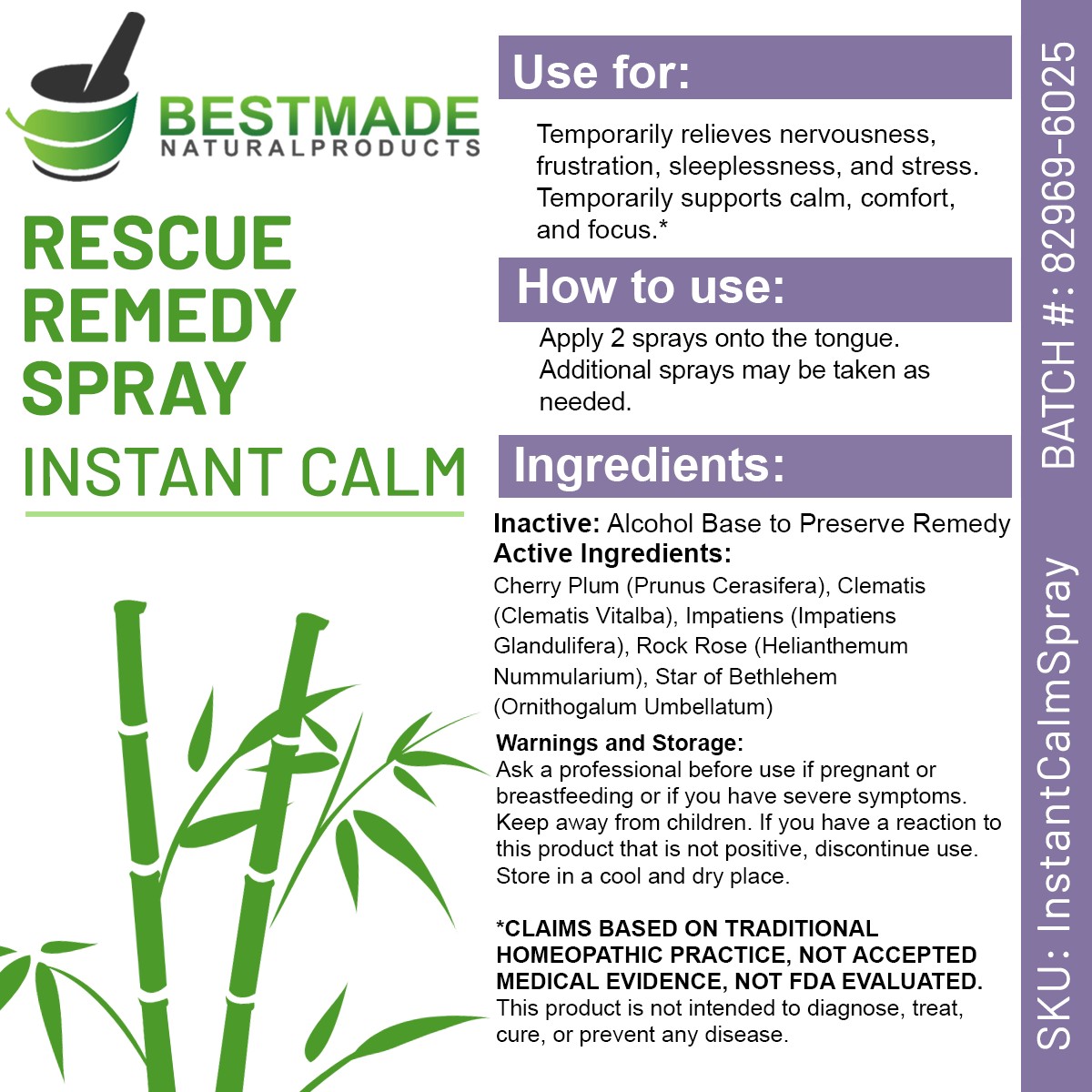 DRUG LABEL: Rescue Remedy (Instant Calm)
NDC: 82969-6025 | Form: SPRAY
Manufacturer: Bestmade Natural Products
Category: homeopathic | Type: HUMAN OTC DRUG LABEL
Date: 20250527

ACTIVE INGREDIENTS: HELIANTHEMUM NUMMULARIUM FLOWER 5 [hp_X]/30 mL; IMPATIENS GLANDULIFERA FLOWER 5 [hp_X]/30 mL; CLEMATIS VITALBA FLOWER 5 [hp_X]/30 mL; ORNITHOGALUM UMBELLATUM BULB 5 [hp_X]/30 mL; PRUNUS CERASIFERA FLOWER 5 [hp_X]/30 mL
INACTIVE INGREDIENTS: ALCOHOL 30 mL/30 mL

Instant Calm Spray (Rescue Remedy Spray)

DOSAGE AND ADMINISTRATION

How to use:
Apply 2 sprays onto the tongue. Additional sprays may be taken as needed.

INACTIVE INGREDIENT

Ingredients:
Inactive: Alcohol Base to Preserve Remedy

INDICATIONS AND USAGE

Use for:

Temporarily relieves nervousness, frustration, sleeplessness, and stress.

Temporarily supports calm, comfort, and focus.*

PURPOSE

Use for:

Temporarily relieves nervousness, frustration, sleeplessness, and stress.

Temporarily supports calm, comfort, and focus.*

Active Ingredients:

Cherry Plum (Prunus Cerasifera)
Clematis (Clematis Vitalba)
Impatiens (Impatiens Glandulifera)
Rock Rose (Helianthemum Nummularium)
Star of Bethlehem (Ornithogalum Umbellatum)

Warnings:

Ask a professional before use if pregnant or breastfeeding or if you have severe symptoms.

Keep away from children. If you have a reaction to this product that is not positive, discontinue use. Store in a cool and dry place

*CLAIMS BASED ON TRADITIONAL HOMEOPATHIC PRACTICE, NOT ACCEPTED MEDICAL EVIDENCE NOT FDA EVALUATED.
This product is not intended to diagnose, treat, cure, or prevent any disease.

Warnings:

Ask a professional before use if pregnant or breastfeeding or if you have severe symptoms.

Keep away from children. If you have a reaction to this product that is not positive, discontinue use. Store in a cool and dry place

*CLAIMS BASED ON TRADITIONAL HOMEOPATHIC PRACTICE, NOT ACCEPTED MEDICAL EVIDENCE NOT FDA EVALUATED.
This product is not intended to diagnose, treat, cure, or prevent any disease.

entire package label